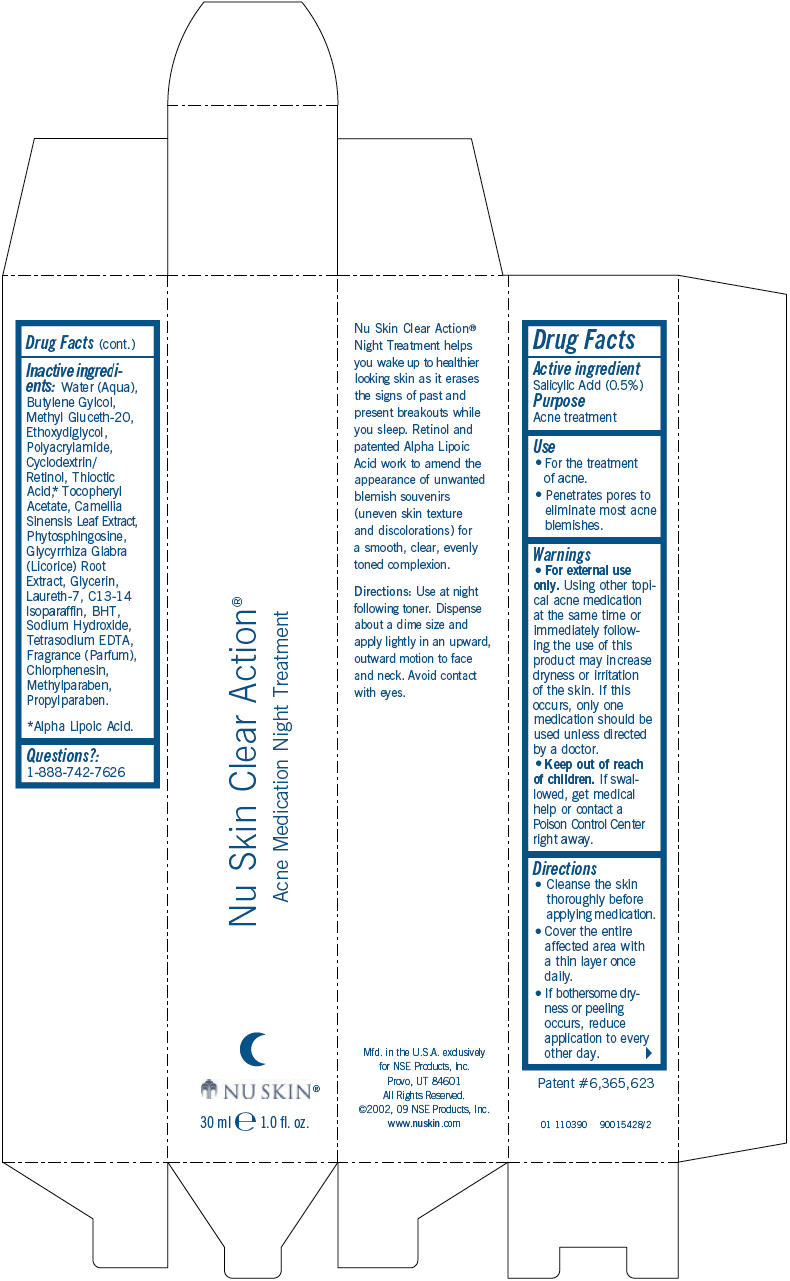 DRUG LABEL: Nu Skin Clear Action 
NDC: 62839-0390 | Form: GEL
Manufacturer: NSE Products, Inc.
Category: otc | Type: HUMAN OTC DRUG LABEL
Date: 20110516

ACTIVE INGREDIENTS: Salicylic Acid 5 g/1000 mL
INACTIVE INGREDIENTS: Water; Butylene Glycol; Methyl Gluceth-20; Diethylene Glycol Monoethyl Ether; Alpha Lipoic Acid; Green Tea Leaf; Glycyrrhiza Glabra; Glycerin; Laureth-7; C13-14 Isoparaffin; Butylated Hydroxytoluene; Sodium Hydroxide; Edetate Sodium; Chlorphenesin; Methylparaben; Propylparaben

Nu Skin Clear Action®
Acne Medication Night Treatment

Drug Facts

Active ingredient

Salicylic Acid (0.5%)

Purpose

Acne treatment

Use

- For the treatment of acne.
- Penetrates pores to eliminate most acne blemishes.

Warnings

WHEN USING

- For external use only. Using other topical acne medication at the same time or immediately following the use of this product may increase dryness or irritation of the skin. If this occurs, only one medication should be used unless directed by a doctor.

- Keep out of reach of children. If swallowed, get medical help or contact a Poison Control Center right away.

Directions

- Cleanse the skin thoroughly before applying medication.
- Cover the entire affected area with a thin layer once daily.
- If bothersome dryness or peeling occurs, reduce application to every other day.

Inactive ingredients

Water (Aqua), Butylene Gylcol, Methyl Gluceth-20, Ethoxydiglycol, Polyacrylamide, Cyclodextrin/Retinol, Thioctic Acid, [Alpha Lipoic Acid.] Tocopheryl Acetate, Camellia Sinensis Leaf Extract, Phytosphingosine, Glycyrrhiza Glabra (Licorice) Root Extract, Glycerin, Laureth-7, C13-14 Isoparaffin, BHT, Sodium Hydroxide, Tetrasodium EDTA, Fragrance (Parfum), Chlorphenesin, Methylparaben, Propylparaben.

Questions?

1-888-742-7626

PRINCIPAL DISPLAY PANEL - 30 ml Carton

Nu Skin Clear Action®

Acne Medication Night Treatment

NU SKIN®

30 ml e 1.0 fl. oz.